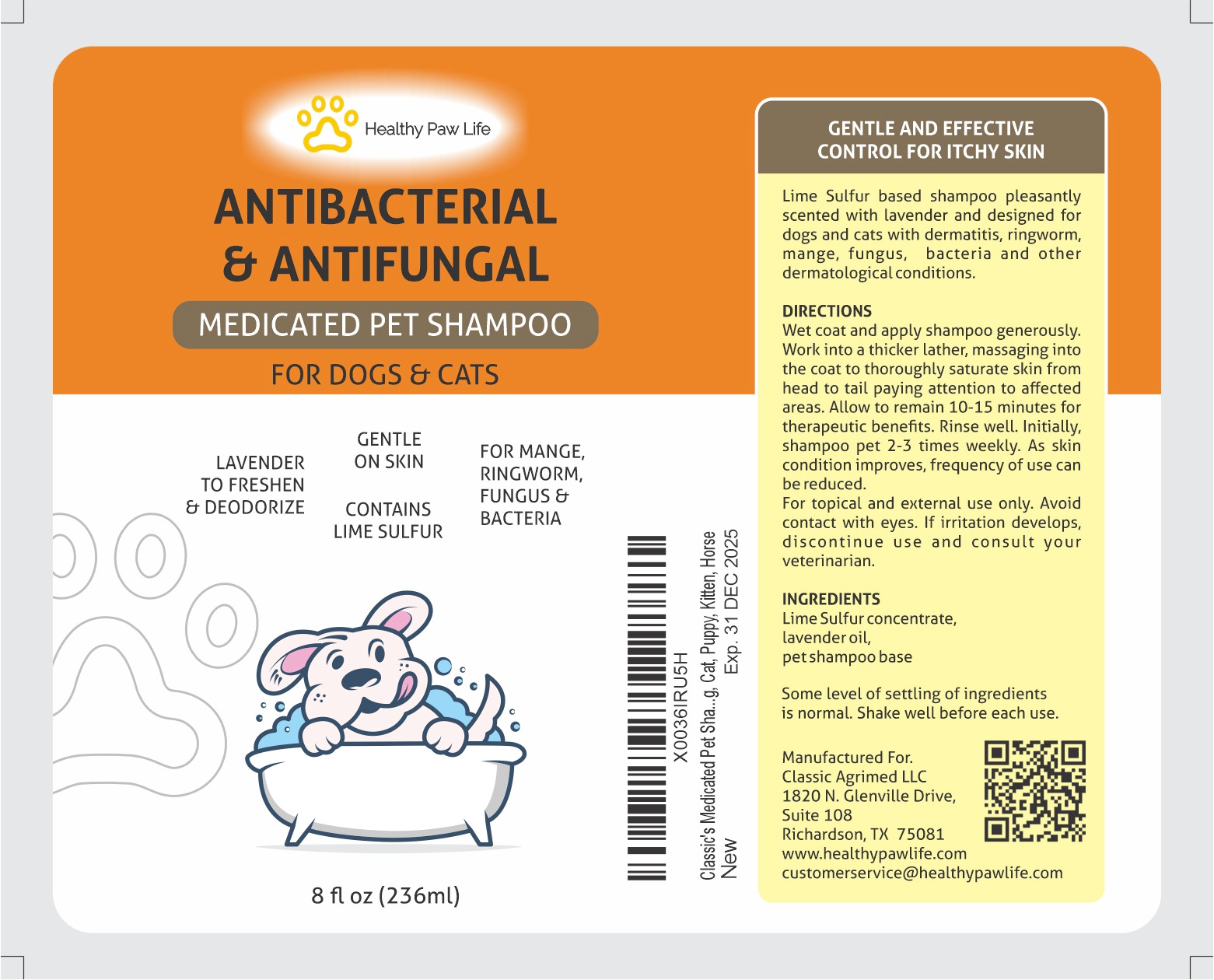 DRUG LABEL: CLASSIC LIME SULFUR
NDC: 86130-401 | Form: SHAMPOO
Manufacturer: CLASSIC AGRIMED LLC
Category: animal | Type: OTC ANIMAL DRUG LABEL
Date: 20231109

ACTIVE INGREDIENTS: CALCIUM POLYSULFIDE 1.45 g/236 g

CLASSIC LIME SULFUR MEDICATED SHAMPOO

Label Description

Lime Sulfur based shampoo pleasantly scented with lavendar and deigned for dogs and cats with dermatitis, ringworm, mange, fungus, bacteria and other dermatological conditions.

DIRECTIONS

Wet coat and apply shampoo generously. Work into a thicker lather, massaging into the coat to thoroughly saturate skin from head to tail paying attention to affected areas. Allow to remain 10-15 minutes for therapeutic benefits. Rinse well. Initially shampoo pet 2-3 times weekly. As skin condition improves, frequency of use can be reduced

For topical and external use only. Avoid contact with eyes. If irritation develops, discontinue use and consult your veterinarian.

INGREDIENTS:

Lime Sulfur concentrate, lavendar oil, pet shampoo base.

Manufactured For:

Classic Agrimed LLC